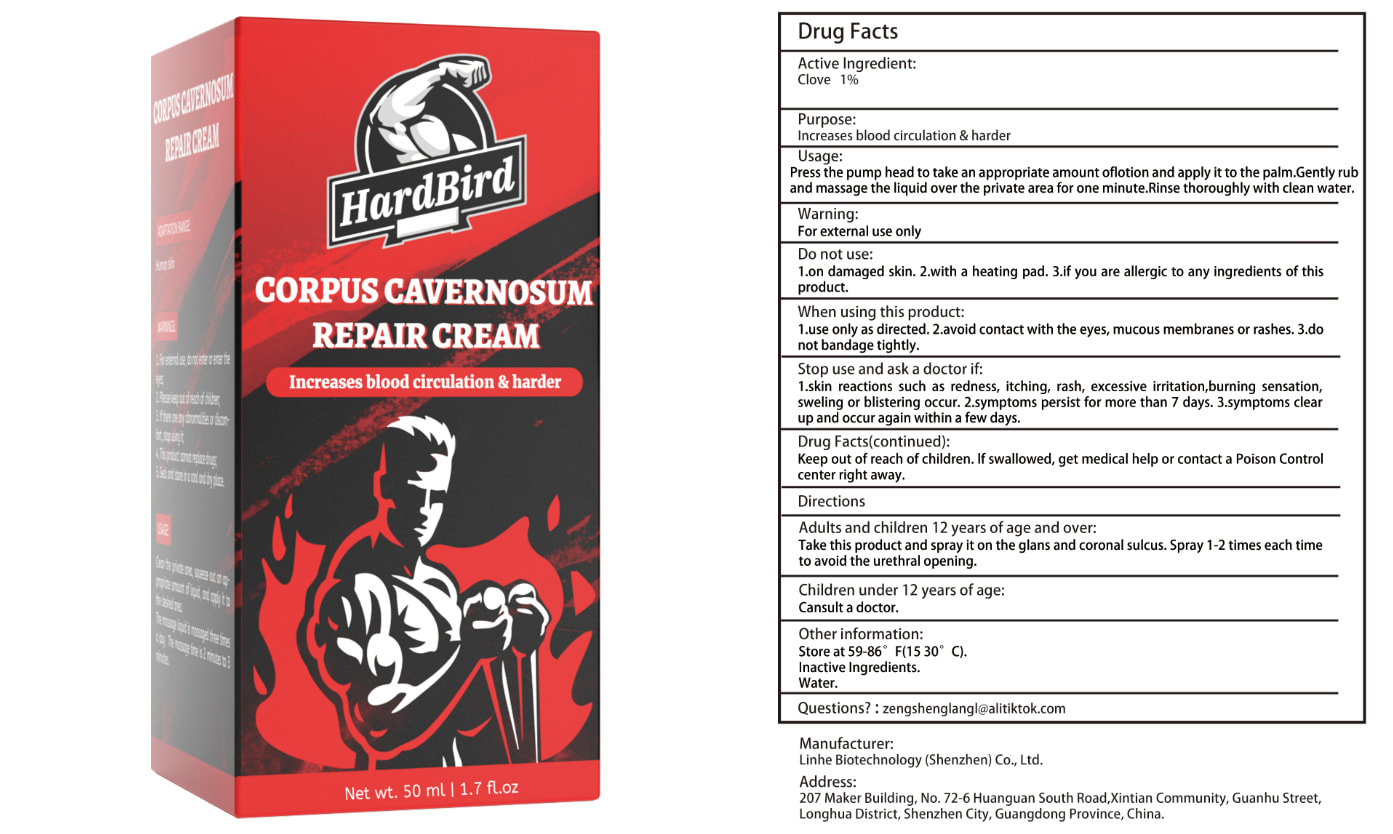 DRUG LABEL: Corpus Cavernosum Repair Cream
NDC: 84575-006 | Form: LIQUID
Manufacturer: Linhe Biotechnology (Shenzhen) Co., Ltd
Category: otc | Type: HUMAN OTC DRUG LABEL
Date: 20240820

ACTIVE INGREDIENTS: CLOVE 1 g/12 mL
INACTIVE INGREDIENTS: GLYCERIN

Corpus Cavernosum Repair Cream

ACTIVE INGREDIENT

Clove 1%

PURPOSE

Increases blood circulation & harder

INDICATIONS AND USAGE

Press the pump head to take an appropriate amount oflotion and apply it to the palm.Gently rub and massage the liquid over the private area for one minute.Rinse thoroughly with clean water.

WARNINGS

For external use only.
Patients with renal failure and those with low heart rates should not use this product. This product is notintended to diagnose,treat, cure or prevent any disease.

DOSAGE AND ADMINISTRATION

Take this product and spray it on the glans and coronal sulcus. Spray 1-2 times each time to avoid the urethral opening.

INACTIVE INGREDIENT

WATER

STORAGE AND HANDLING

Store in a cool and dark place away from light

Keep out of reach of children,in case of overdose, get medical help or contact a PoisonControl Center right away.